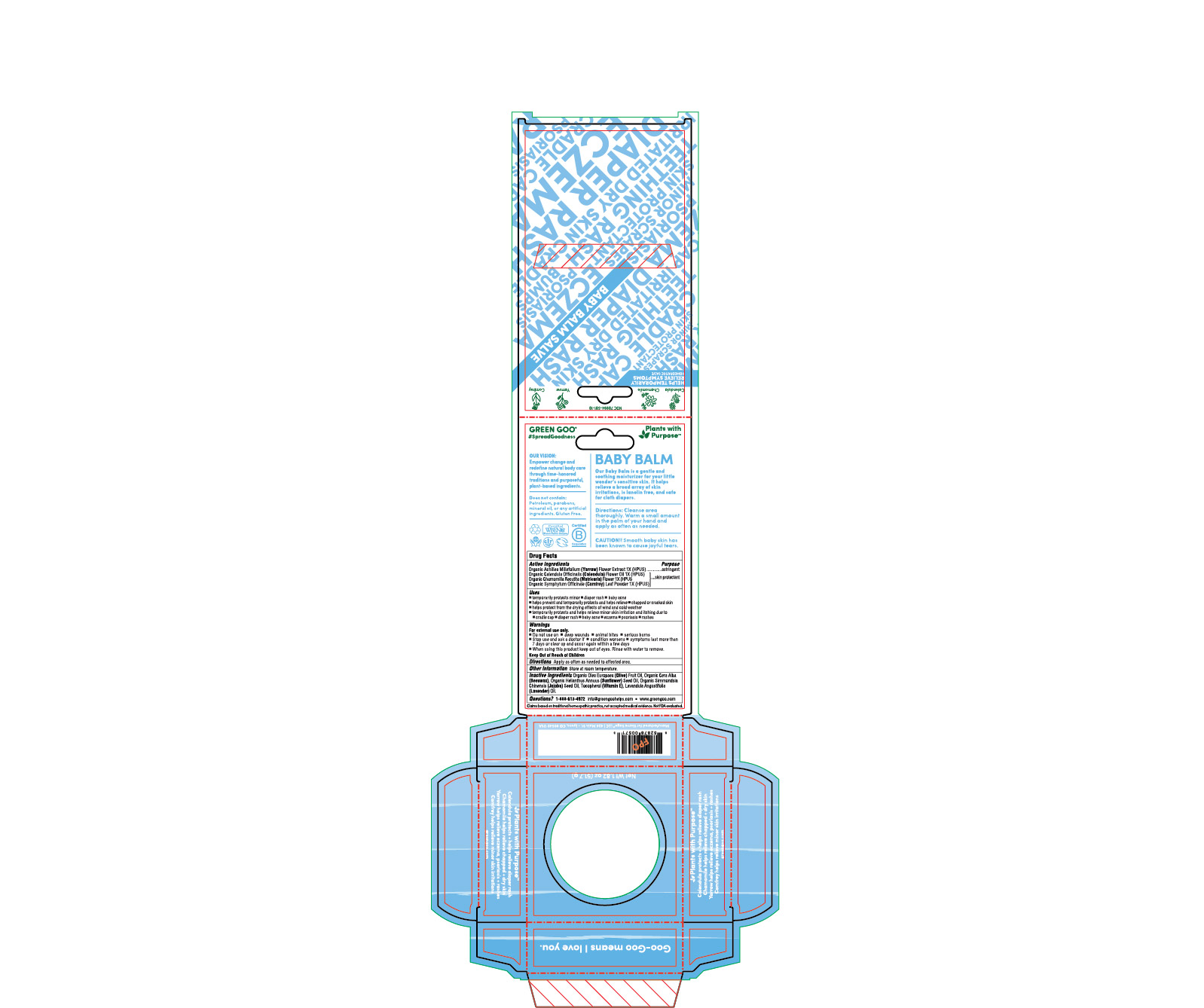 DRUG LABEL: Baby Balm
NDC: 70994-501 | Form: SALVE
Manufacturer: Spry Life LLC
Category: homeopathic | Type: HUMAN OTC DRUG LABEL
Date: 20251215

ACTIVE INGREDIENTS: CALENDULA OFFICINALIS FLOWER 1 [hp_X]/51.7 g; SYMPHYTUM OFFICINALE WHOLE 1 [hp_X]/51.7 g; CHAMOMILE 1 [hp_X]/51.7 g; ACHILLEA MILLEFOLIUM FLOWER 1 [hp_X]/51.7 g
INACTIVE INGREDIENTS: YELLOW WAX; ALPHA-TOCOPHEROL; LAVENDER OIL; JOJOBA OIL; OLIVE OIL; SUNFLOWER OIL

Baby Balm

OTC Purpose

Skin Protectant

Astringent

OTC Active Ingredients

Organic Achillea Millefolium (Yarrow) Flower Extract 1X (HPUS)

Organic Calendula Officinalis (Calendula) Flower Oil 1X (HPUS)

Organic Chamomilla Recutita (Matricaria) Flower 1X (HPUS
Organic Symphytum Officinale (Comfrey) Leaf Powder 1X (HPUS)

Indications & Usage

-temporarily protects minor • diapar rash • baby acne

-helps prevent and temporarily protects and helps relieve • chapped or cracked skin

-helps protect from the drying effects of wind and cold weather

-temporarily protects and helps relieve minor skin irritation and itching due to • cradle cap • diaper rash • baby acne • eczema • psoriasis • rashes

Warnings

For external use only.

-Do not use on • on deep wounds • animal bites • serious burns

-Stop use and ask a doctor if • condition worsens • symptoms last more than 7 days or clear up and occur again within a few days

-When using this product keep out of eyes. Rinse with water to remove.

Keep Out of Reach of Children

Storage and Handlin

Store at room temperature.

Dosage & Administration

Apply as often as needed to the affected area.

Inactive Ingredients

Organic Olea Europaea(Olive) Fruit Oil,Organic Cera Alba (Beeswax), Organic Helianthus Annuus (Sunflower) Seed Oil, Organic Simmondsia Chinensis (Jojoba) Seed Oil, Tocopherol (Vitamin E), Lavandula Angustifolia (Lavender) Oil.